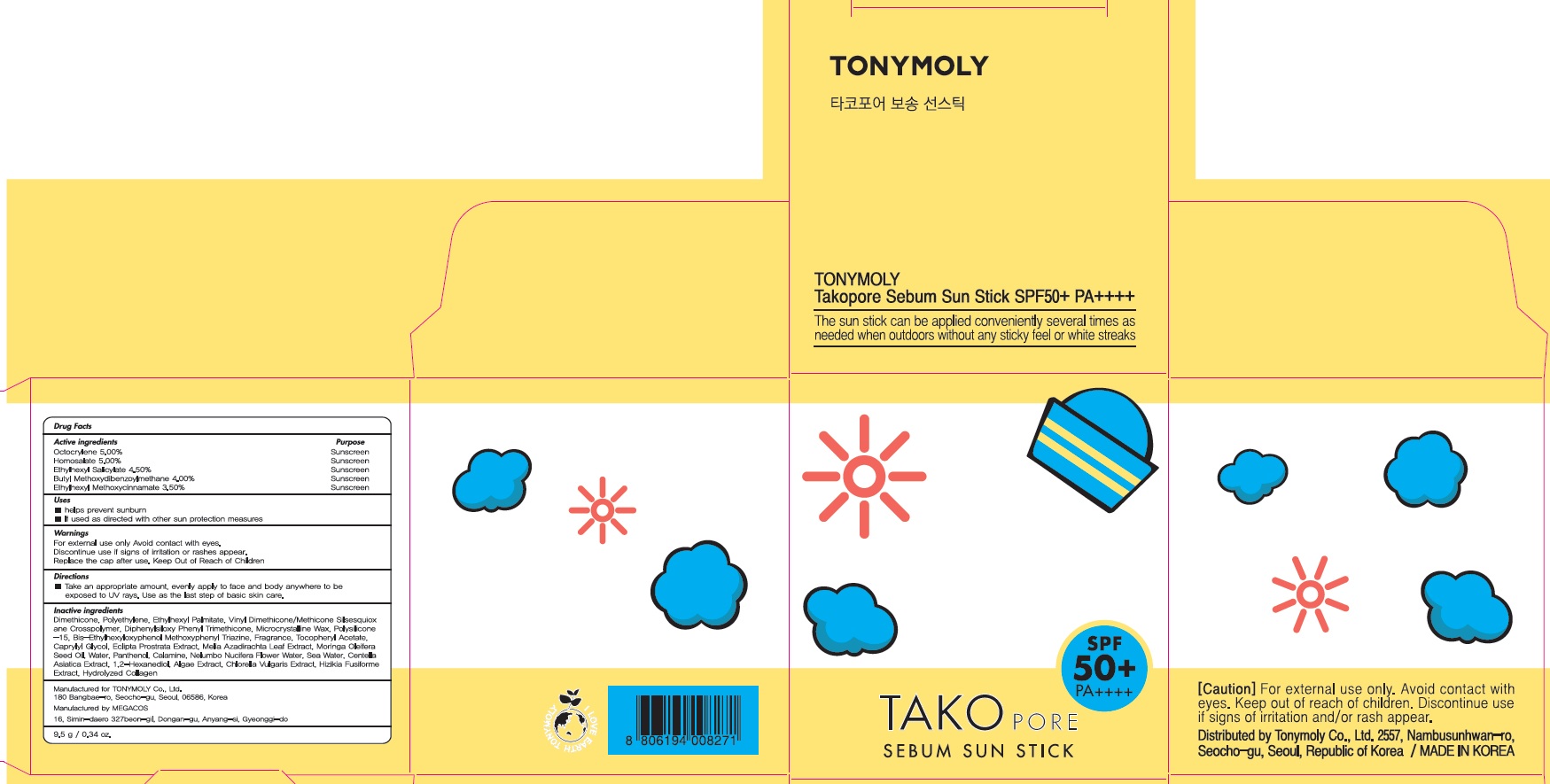 DRUG LABEL: TAKO PORE SEBUM SUN
NDC: 59078-326 | Form: STICK
Manufacturer: TONY MOLY CO.,LTD
Category: otc | Type: HUMAN OTC DRUG LABEL
Date: 20180404

ACTIVE INGREDIENTS: Octocrylene 0.47 g/9.5 g; Homosalate 0.47 g/9.5 g; Octisalate 0.42 g/9.5 g; Avobenzone 0.38 g/9.5 g; Octinoxate 0.33 g/9.5 g
INACTIVE INGREDIENTS: Dimethicone; Ethylhexyl Palmitate

ACTIVE INGREDIENT

Active ingredients: Octocrylene 5.00%, Homosalate 5.00%, Ethylhexyl Salicylate 4.50%, Butyl Methoxydibenzoylmethane 4.00%, Ethylhexyl Methoxycinnamate 3.50%

INACTIVE INGREDIENT

Inactive ingredients:

Dimethicone, Polyethylene, Ethylhexyl Palmitate, Vinyl Dimethicone/Methicone Silsesquioxane Crosspolymer, Diphenylsiloxy Phenyl Trimethicone, Microcrystalline Wax, Polysilicone-15, Bis-Ethylhexyloxyphenol Methoxyphenyl Triazine, Fragrance, Tocopheryl Acetate, Caprylyl Glycol, Eclipta Prostrata Extract, Melia Azadirachta Leaf Extract, Moringa Oleifera Seed Oil, Water, Panthenol, Calamine, Nelumbo Nucifera Flower Water, Sea Water, Centella Asiatica Extract, 1,2-Hexanediol, Algae Extract, Chlorella Vulgaris Extract, Hizikia Fusiforme Extract, Hydrolyzed Collagen

PURPOSE

Purpose: Sunscreen

WARNINGS

For external use only

Avoid contact with eyes.

Discontinue use if signs of irritation or rashes appear.

Replace the cap after use.

Keep Out of Reach of Children

DESCRIPTION

Uses:

- helps prevent sunburn

- If used as directed with other sun protection measures

Directions:

Take an appropriate amount, evenly apply to face and body anywhere to be exposed to UV rays. Use as the last step of basic skin care.